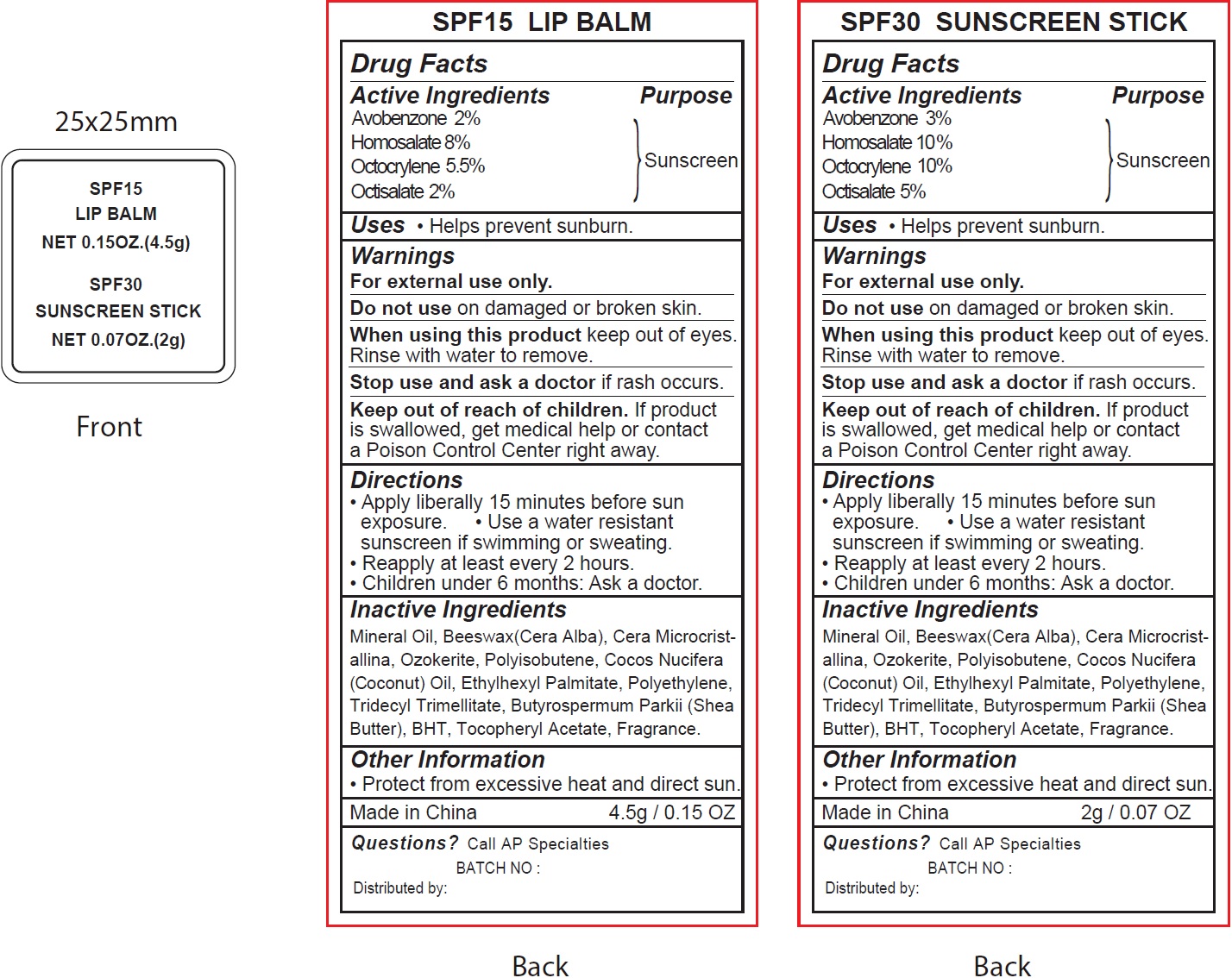 DRUG LABEL: SPF 15 Lip and SPF 30 Sunscreen
NDC: 70412-819 | Form: KIT | Route: TOPICAL
Manufacturer: Zhejiang Ayan Biotech Co.,Ltd.
Category: otc | Type: HUMAN OTC DRUG LABEL
Date: 20231120

ACTIVE INGREDIENTS: AVOBENZONE 20 mg/1 g; HOMOSALATE 80 mg/1 g; OCTOCRYLENE 55 mg/1 g; OCTISALATE 20 mg/1 g; AVOBENZONE 30 mg/1 g; HOMOSALATE 100 mg/1 g; OCTOCRYLENE 100 mg/1 g; OCTISALATE 50 mg/1 g
INACTIVE INGREDIENTS: MINERAL OIL; YELLOW WAX; CERESIN; COCONUT OIL; ETHYLHEXYL PALMITATE; HIGH DENSITY POLYETHYLENE; TRIDECYL TRIMELLITATE; SHEA BUTTER; BUTYLATED HYDROXYTOLUENE; .ALPHA.-TOCOPHEROL ACETATE; MINERAL OIL; YELLOW WAX; CERESIN; COCONUT OIL; ETHYLHEXYL PALMITATE; HIGH DENSITY POLYETHYLENE; TRIDECYL TRIMELLITATE; SHEA BUTTER; BUTYLATED HYDROXYTOLUENE; .ALPHA.-TOCOPHEROL ACETATE

SPF 15 Lip Balm and SPF 30Sunscreen Stick

Active Ingredients

Homosalate 2%
Avobenzone 8%
Octocrylene 5.5%
Octisalate 2%

Purpose

Sunscreen

Uses

• Helps prevent sunburn.

Warnings

For external use only.

Do not use

on damaged or broken skin.

When using this product

keep out of eyes. Rinse with water to remove.

Stop use and ask a doctor

if rash occurs.

Keep out of reach of children.

If product is swallowed, get medical help or contact a Poison Control Center right away.

Directions

• Apply liberally 15 minutes before sun exposure. • Use a water resistant sunscreen if swimming or sweating.
• Reapply at least every 2 hours.
• Children under 6 months: Ask a doctor.

Inactive Ingredients

Mineral Oil, Beeswax(Cera Alba), Cera Microcristallina, Ozokerite, Polyisobutene, Cocos Nucifera (Coconut) Oil, Ethylhexyl Palmitate, Polyethylene, Tridecyl Trimellitate, Butyrospermum Parkii (Shea Butter), BHT, Tocopheryl Acetate, Fragrance.

Other Information

• Protect from excessive heat and direct sun.

Questions?

Call AP Specialties

Active Ingredients

Homosalate 2%
Avobenzone 8%
Octocrylene 5.5%
Octisalate 2%

Purpose

Sunscreen

Uses

• Helps prevent sunburn.

Warnings

For external use only.

Do not use

on damaged or broken skin.

When using this product

keep out of eyes. Rinse with water to remove.

Stop use and ask a doctor

if rash occurs.

Keep out of reach of children.

If product is swallowed, get medical help or contact a Poison Control Center right away.

Directions

• Apply liberally 15 minutes before sun exposure. • Use a water resistant sunscreen if swimming or sweating.
• Reapply at least every 2 hours.
• Children under 6 months: Ask a doctor.

Inactive Ingredients

Mineral Oil, Cera Microcristallina, Polyisobutene, Cocos Nucifera (Coconut) Oil, Ethylhexyl Palmitate, Polyethylene, Hydroxystearic Acid, Butyrospermum Parkii (Shea Butter), Tridecyl Trimellitate, Ozokerite, Synthetic Wax, Dextrin Palmitate, BHT, Tocopheryl Acetate, Fragrance.

Other Information

• Protect from excessive heat and direct sun.

Questions?

Call AP Specialties